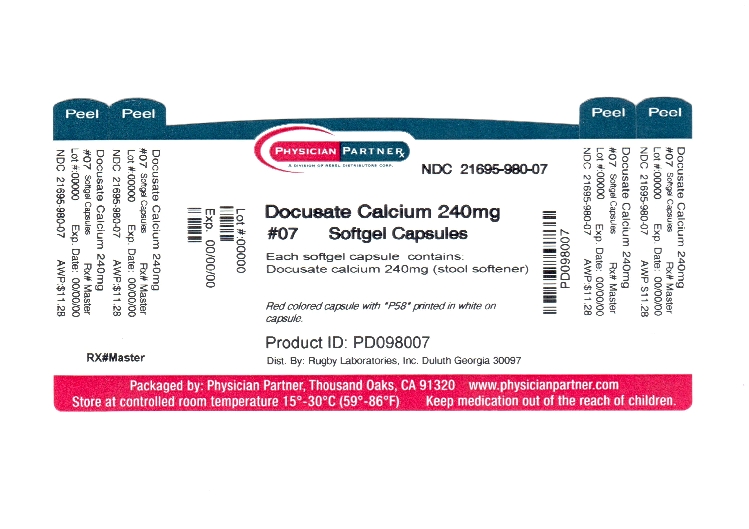 DRUG LABEL: Docusate Calcium
NDC: 21695-980 | Form: CAPSULE
Manufacturer: Rebel Distributors Corp
Category: otc | Type: HUMAN OTC DRUG LABEL
Date: 20110907

ACTIVE INGREDIENTS: DOCUSATE CALCIUM 240 mg/1 1
INACTIVE INGREDIENTS: CORN OIL; D&C RED NO. 33; FD&C RED NO. 40; GELATIN; GLYCERIN; WATER; SORBITOL

Docusate Calcium

Active ingredient(s)

Docusate Calcium

Purpose

Stool Softener

Use(s)

for relief of occasional constipation. This product generally produces a bowel movement within 12 to 72 hours.

Warnings

-Do not use if you are currently taking mineral oil, unless directed by a doctor

-When abdominal pain, nausea, or vomiting are present

-For longer than 1 week, unless directed by a doctor

Ask a doctor before use if

You notice a sudden change in bowel habits that persists over a period of 2 weeks.

Ask a doctor or pharmacist before use if

You notice a sudden change in bowel habits that persists over a period of 2 weeks.

Stop use and ask a doctor if

-You have rectal bleeding

-you fail to have a bowel movement after use

Pregnancy/Breastfeeding

Ask a health care professional before use.

Keep out of reach of children

In case of overdose, get medical help or contact a Poison Control Center right away.

Directions

-adults and children over 12 years of age: take 1 softgel daily for several days, or until bowel movements are normal, or as directed by a doctor

-children under 12 years of age: take as directed by a doctor

Other information

-do not use if imprinted safety seal under cap is broken or missing

-This product is not manufactured or distributed by Chattem, Inc., owner of the registered trademark Surfak Stool Softener

Storage

Store at controlled room temperature 15 degrees-30 degrees C (59 degrees-86 degrees F)

Inactive ingredients

Corn oil, D&C Red #33, FD&C Red #40, gelatin, glycerin, purified water and sorbitol special.

Questions

Adverse Drug Event Call: (800) 616-2471

Distributed by: Rugby Laboratories, Inc. Duluth GA 30097

Repackaged by: Rebel Distributors Corp Thousand Oaks, CA 91320

Principal Display Panel

Docusate Calcium Softgel Capsules

240mg